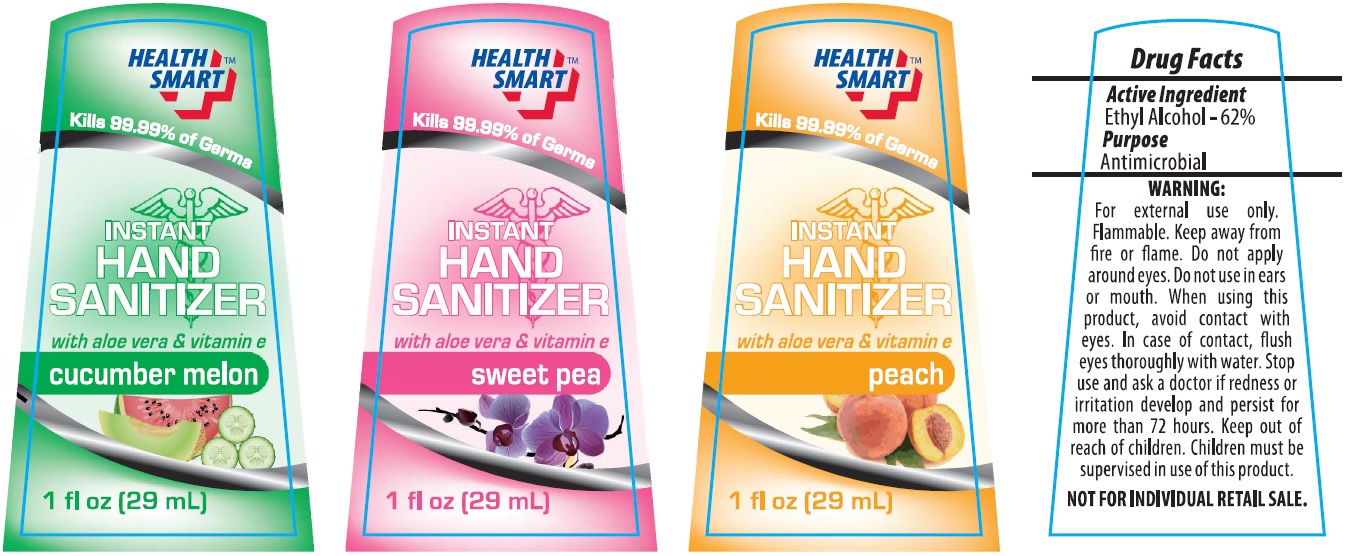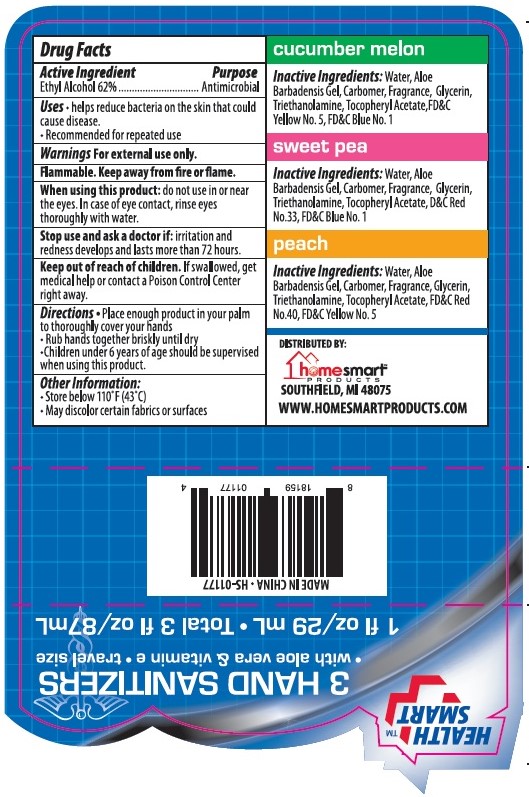 DRUG LABEL: 3 HAND SANITIZERS
NDC: 52862-412 | Form: KIT | Route: TOPICAL
Manufacturer: International Wholesale, Inc.
Category: otc | Type: HUMAN OTC DRUG LABEL
Date: 20141115

ACTIVE INGREDIENTS: ALCOHOL 62 mL/100 mL; ALCOHOL 62 mL/100 mL; ALCOHOL 62 mL/100 mL
INACTIVE INGREDIENTS: WATER; ALOE VERA LEAF; CARBOMER HOMOPOLYMER TYPE C (ALLYL PENTAERYTHRITOL CROSSLINKED) ; GLYCERIN; TROLAMINE; .ALPHA.-TOCOPHEROL ACETATE; FD&C YELLOW NO. 5; FD&C BLUE NO. 1; WATER; ALOE VERA LEAF; CARBOMER HOMOPOLYMER TYPE C (ALLYL PENTAERYTHRITOL CROSSLINKED) ; GLYCERIN; TROLAMINE; .ALPHA.-TOCOPHEROL ACETATE; D&C RED NO. 33; FD&C BLUE NO. 1; WATER; ALOE VERA LEAF; CARBOMER HOMOPOLYMER TYPE C (ALLYL PENTAERYTHRITOL CROSSLINKED) ; GLYCERIN; TROLAMINE; .ALPHA.-TOCOPHEROL ACETATE; D&C RED NO. 33; FD&C BLUE NO. 1

Drug Facts

Active Ingredients

Ethyl Alcohol 62%

Purpose

Antimicrobial

Uses

- helps reduce bacteria on the skin that could cause disease
- Recommended for repeated use

Warnings

For external use only.

Flammable. Keep away from fire or flame.

When using this product do not use in or near the eyes. In case of eye contact, rinse eyes thoroughly with water.

Stop use and ask a doctor if: irritation and redness develops and lasts more than 72 hours.

Keep out of reach of children. If swallowed, get medical help or contact a Poison Control Center right away.

Directions

- Place enough product in your palm to thoroughly cover your hands
- Rub hands together briskly until dry
- Children under 6 years of age should be supervised when using this product.

Other information

- Store below 110°F (43°C)
- May discolor certain fabrics or surfaces.

cucumber melon

Inactive ingredients Water, Aloe Barbadensis Gel, Carbomer, Glycerin, Triethanolamine, Tocopheryl Acetate, FD&C Yellow No. 5, FD&C Blue No.1

sweet pea

Inactive ingredients Water, Aloe Barbadensis Gel, Carbomer, Glycerin, Triethanolamine, Tocopheryl Acetate, D&C Red No. 33, FD&C Blue No.1

peach

Inactive ingredients Water, Aloe Barbadensis Gel, Carbomer, Glycerin, Triethanolamine, Tocopheryl Acetate, FD&C Red No. 40, FD&C Yellow No. 5

MADE IN CHINA.

DISTRIBUTED BY:
homesmartTM
PRODUCTS
SOUTHFIELD, MI 48075
WWW.HOMESMARTPRODUCTS.COM

NOT FOR INDIVIDUAL SALE

PACKAGE LABEL

HEALTH SMARTTM
3 HAND SANITIZERS
• with aloe vera & vitamin e •travel size
1 fl oz/29 ml • Total 3 fl oz/ 87 mL